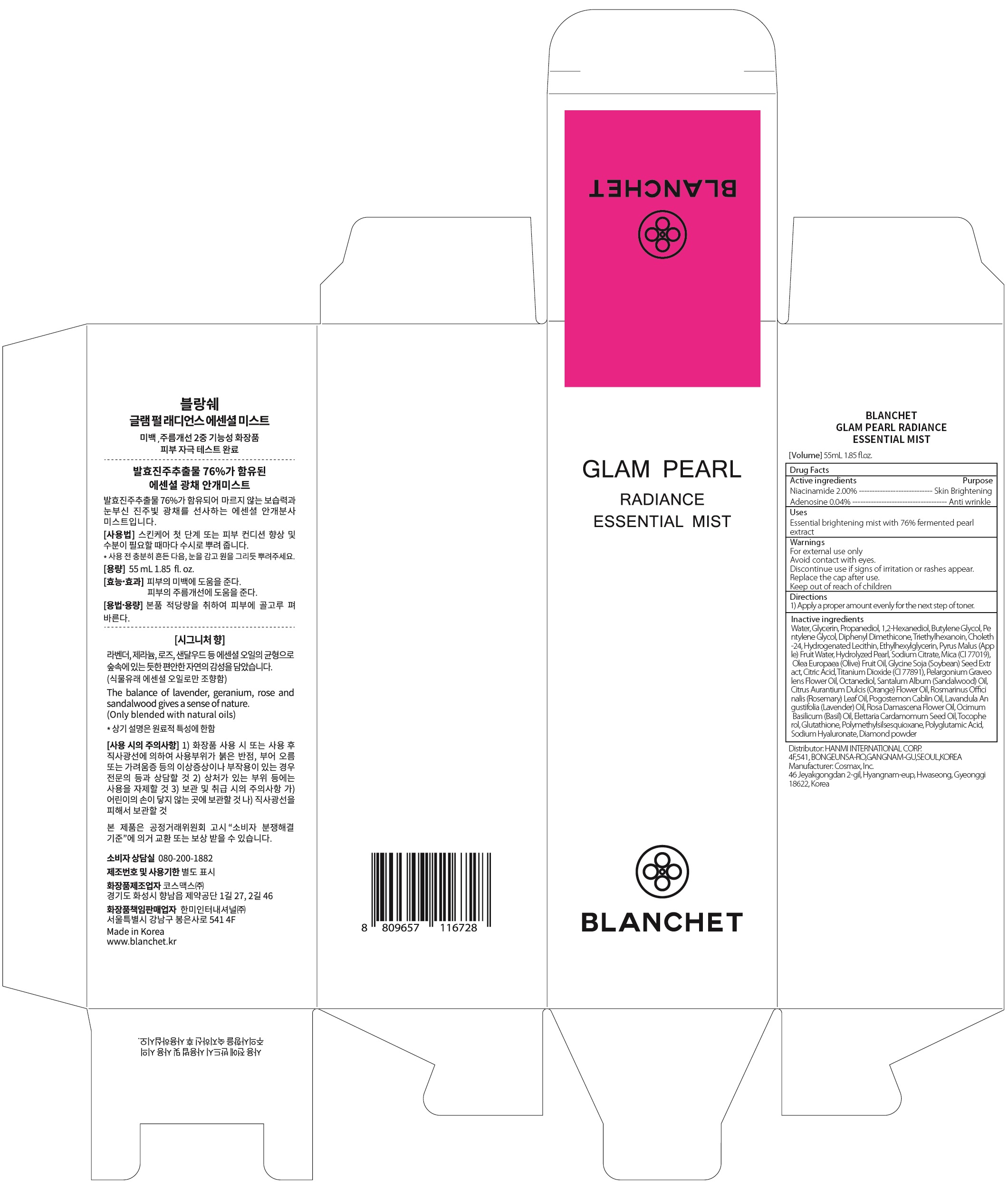 DRUG LABEL: BLANCHET GLAM PEARL RADIANCE ESSENTIAL MIST
NDC: 79171-020 | Form: SPRAY
Manufacturer: Hanmi International Corp.
Category: otc | Type: HUMAN OTC DRUG LABEL
Date: 20200806

ACTIVE INGREDIENTS: Niacinamide 1.1 g/55 mL; Adenosine 0.02 g/55 mL
INACTIVE INGREDIENTS: Water; Glycerin; Propanediol

ACTIVE INGREDIENTS

Niacinamide 2.00%
Adenosine 0.04%

PURPOSE

Skin Brightening
Anti wrinkle

Uses

Essential brightening mist with 76% fermented pearl extract

WARNINGS

For external use only
Avoid contact with eyes.
Discontinue use if signs of irritation or rashes appear.
Replace the cap after use.
Keep out of reach of children

KEEP OUT OF REACH OF CHILDREN

Directions

Apply a proper amount evenly for the next step of toner.

INACTIVE INGREDIENTS

Water, Glycerin, Propanediol, 1,2-Hexanediol, Butylene Glycol, Pentylene Glycol, Diphenyl Dimethicone, Triethylhexanoin, Choleth-24, Hydrogenated Lecithin, Ethylhexylglycerin, Pyrus Malus (Apple) Fruit Water, Hydrolyzed Pearl, Sodium Citrate, Mica (CI 77019), Olea Europaea (Olive) Fruit Oil, Glycine Soja (Soybean) Seed Extract, Citric Acid, Titanium Dioxide (CI 77891), Pelargonium Graveolens Flower Oil, Octanediol, Santalum Album (Sandalwood) Oil, Citrus Aurantium Dulcis (Orange) Flower Oil, Rosmarinus Officinalis (Rosemary) Leaf Oil, Pogostemon Cablin Oil, Lavandula Angustifolia (Lavender) Oil, Rosa Damascena Flower Oil, Ocimum Basilicum (Basil) Oil, Elettaria Cardamomum Seed Oil, Tocopherol, Glutathione, Polymethylsilsesquioxane, Polyglutamic Acid, Sodium Hyaluronate, Diamond powder